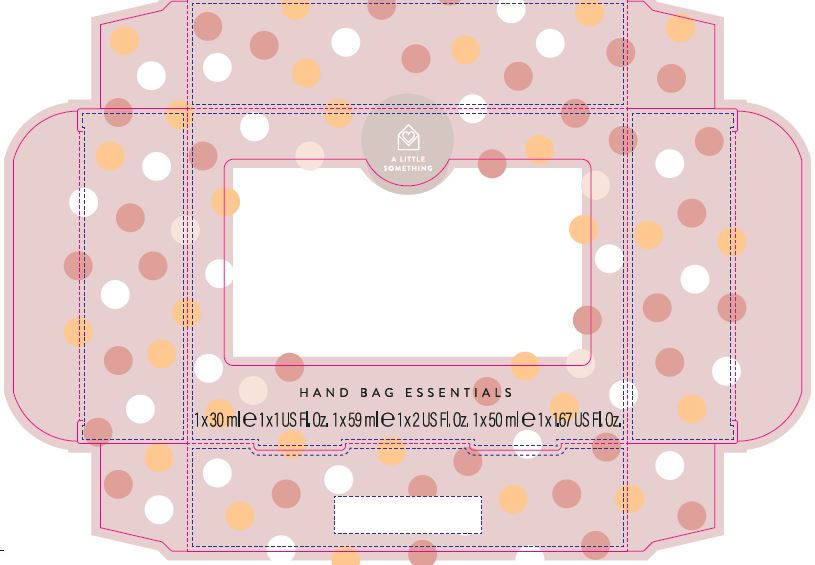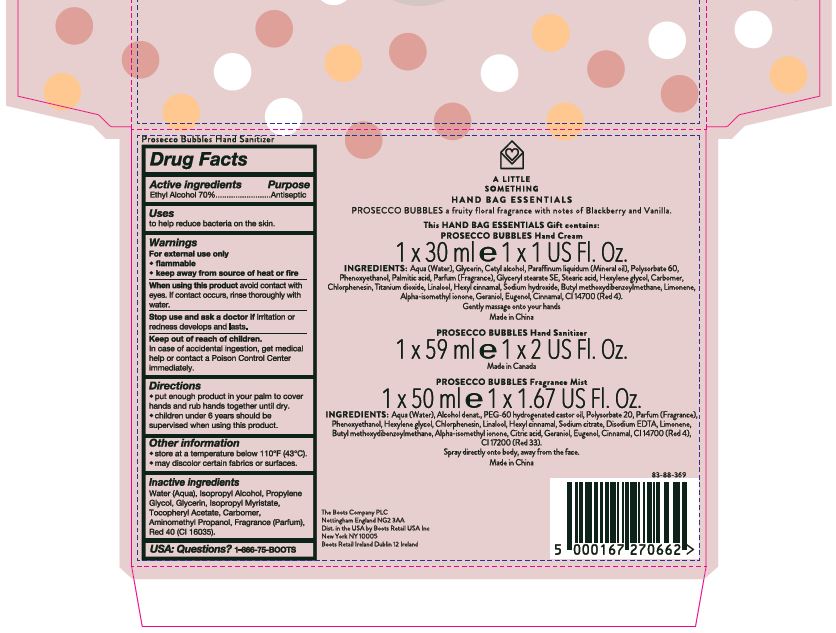 DRUG LABEL: A Little Something Prosecco Bubbles Hand Sanitizer
NDC: 0363-1051 | Form: LIQUID
Manufacturer: Walgreen Company
Category: otc | Type: HUMAN OTC DRUG LABEL
Date: 20201217

ACTIVE INGREDIENTS: ALCOHOL 700 mg/1 mL
INACTIVE INGREDIENTS: WATER; ISOPROPYL ALCOHOL; PROPYLENE GLYCOL; GLYCERIN; ISOPROPYL MYRISTATE; .ALPHA.-TOCOPHEROL ACETATE, DL-; CARBOMER 934; AMINOMETHYLPROPANOL; FD&C RED NO. 40

A Little Something Hand Bag Essentials - Prosecco Bubbles

Active ingredients

Ethyl Alcohol 70%

Purpose

Pupose

Antiseptic

Uses

to help reduce bacteria on the skin.

Warnings

For external use only

flammable

keep away fro source of heat or fire

When using

When using this product avoid contact with eyes. If contact occurs, rinse thoroughly with water.

Stop use

Stop use and ask a doctor if irritation or redness develops and lasts.

Keep out of reach of children

In case of accidental ingestion, get medical help or contact a Poison Control Center immediately.

Directions

put enough product in your palm to cover hands and rub hands together until dry.

children under 6 years should be supervised when using this product.

Inactive ingredients

Water (Aqua), Isopropyl Alcohol, Propylene Glycol, Glycerin, Isopropyl Myristate, Tocopheryl Acetate, Carbomer, Aminomethyl Propanol, Fragrance (Parfum), Red 40 (CI 16035).

Questions

USA: Questions? 1-866075-BOOTS

Other information

store at a temperature below 110F (43C).

may discolor certain fabrics or surfaces.

Description

A Little Something

Hand Bag Essentials

1 x 59 ml e 1 x 2 US Fl. Oz.

This Hand Bag Essentials Gift contains:

PROSECCO BUBBLES Hand Sanitizer

1 x 59 ml e 1 x 2 US Fl. Oz.

Made in Canada

The Boots Company PLC

Nottingham England NG2 3AA

Dist. in the USA by Boots Retail USA Inc

New York NY 10005

Boots Retail Ireland Dublin 12 Ireland

Carton